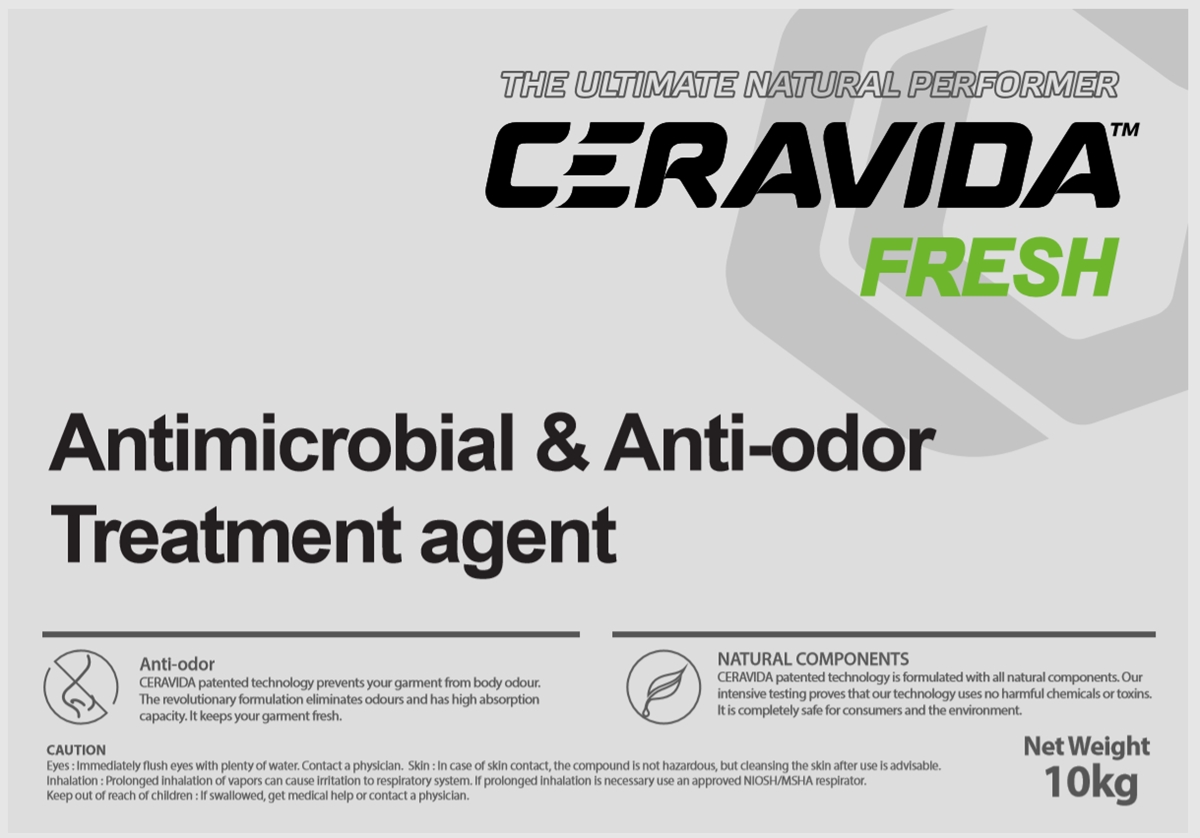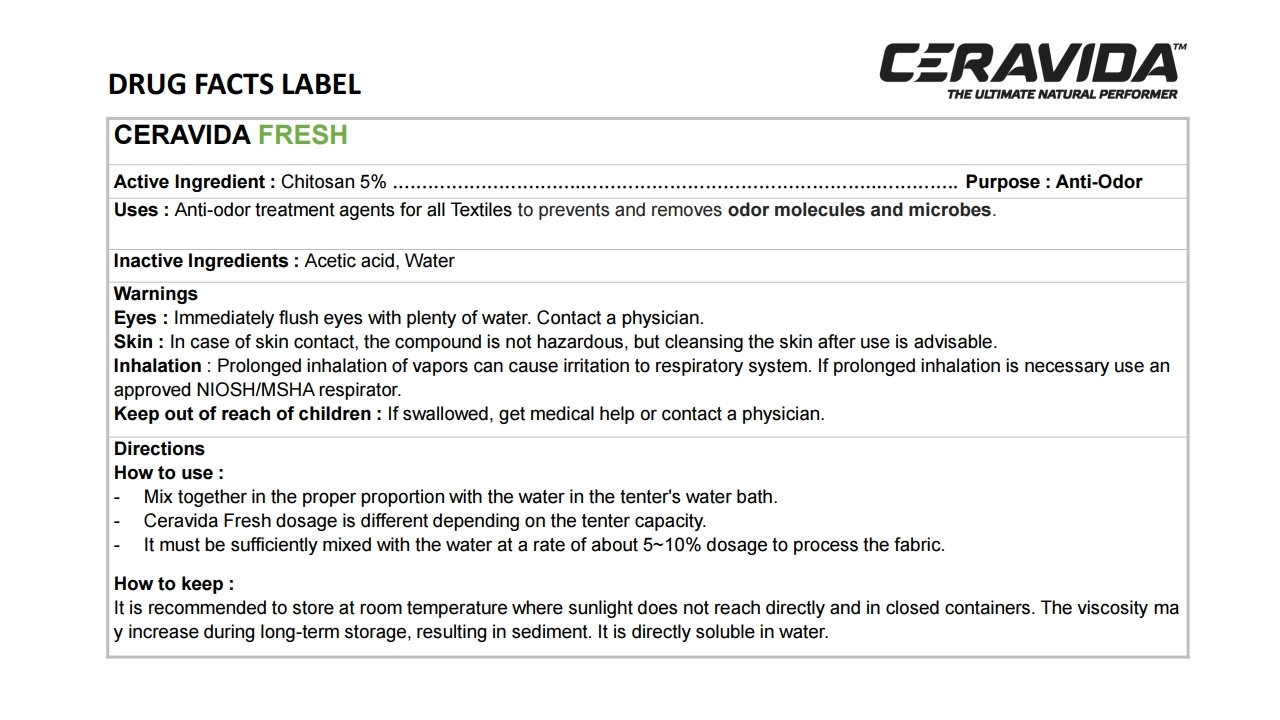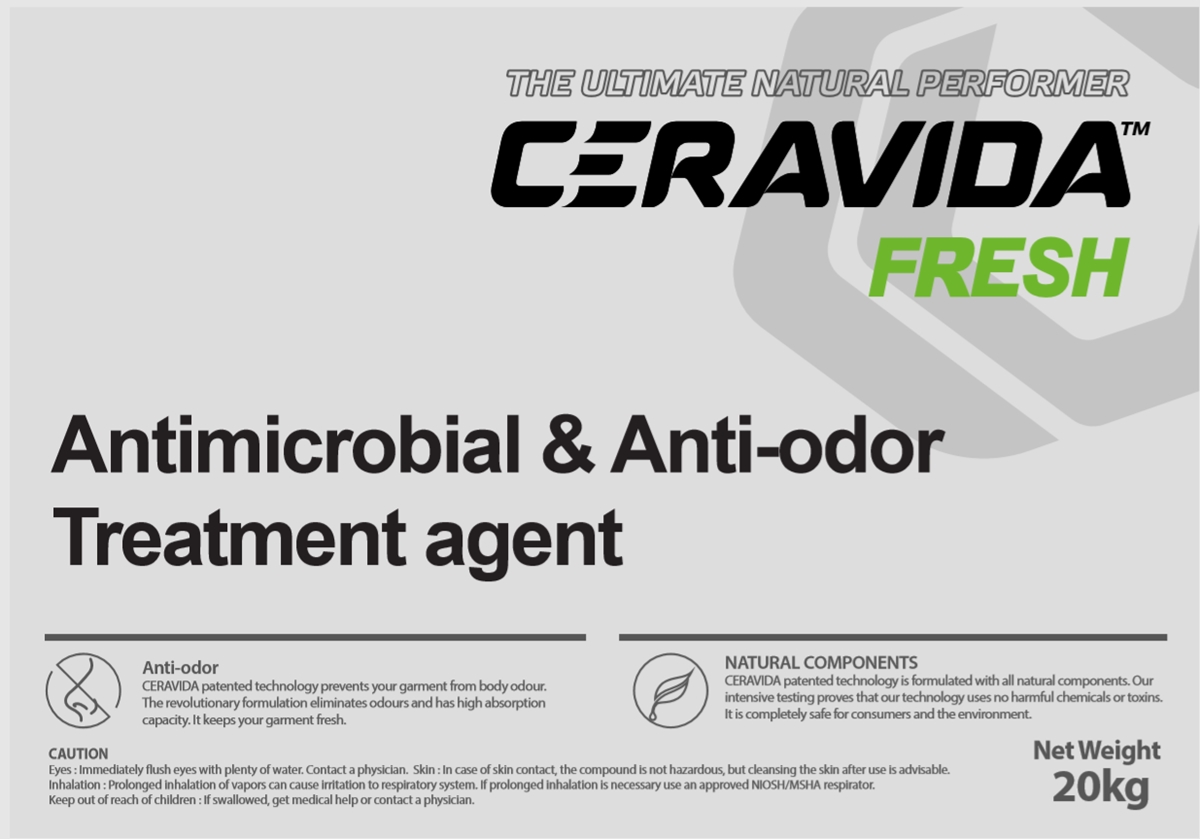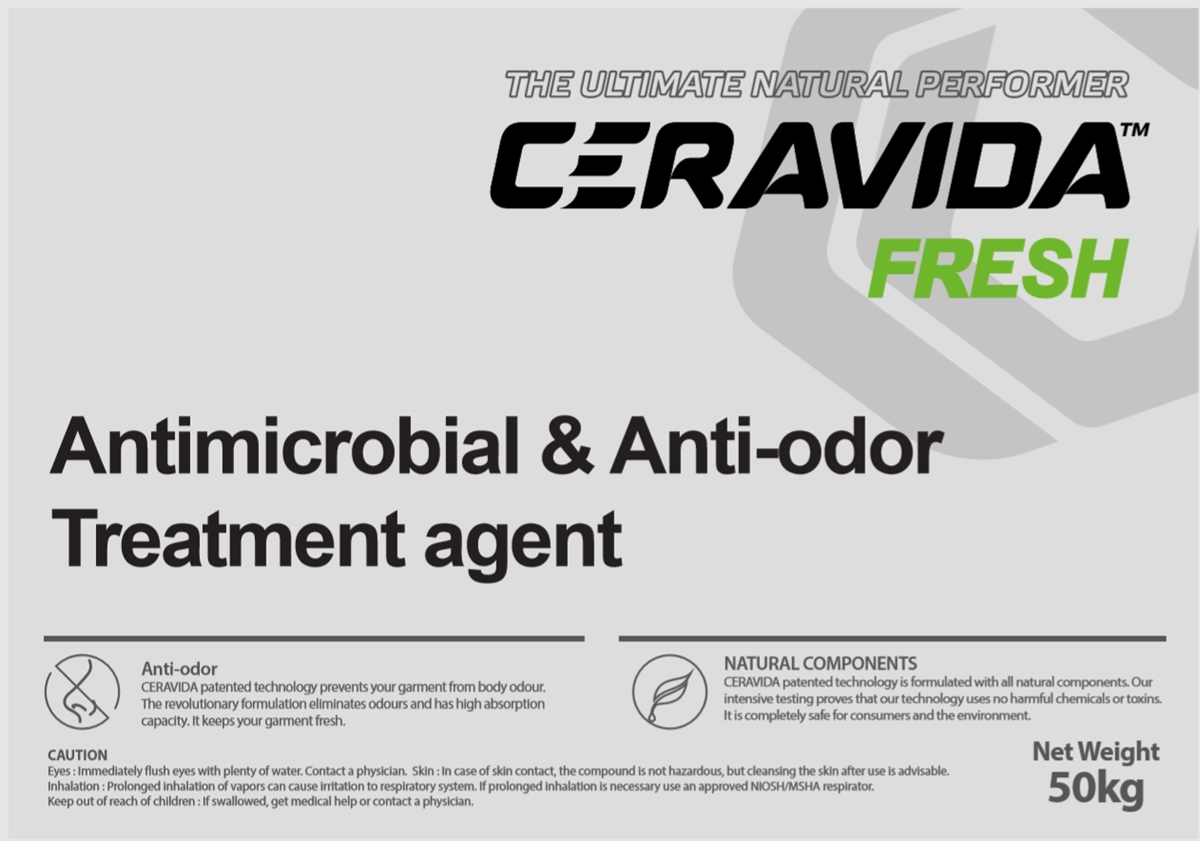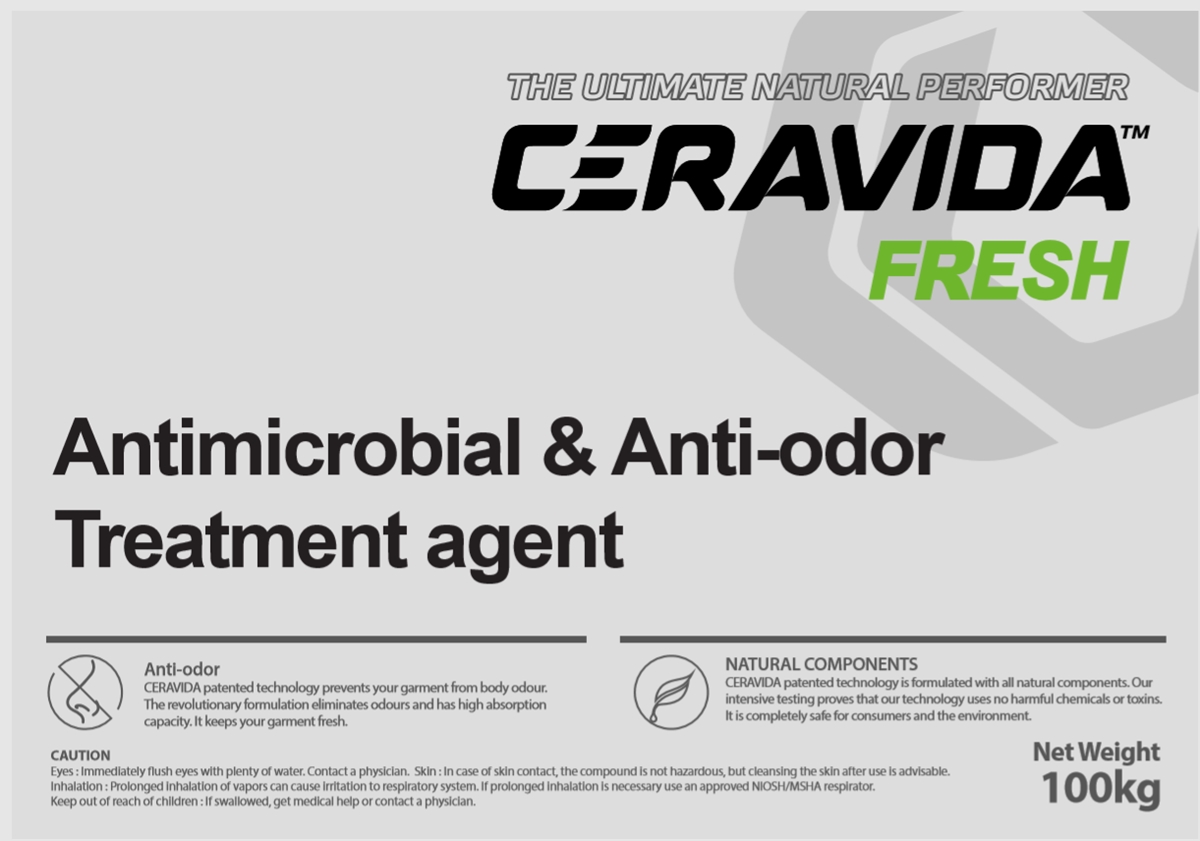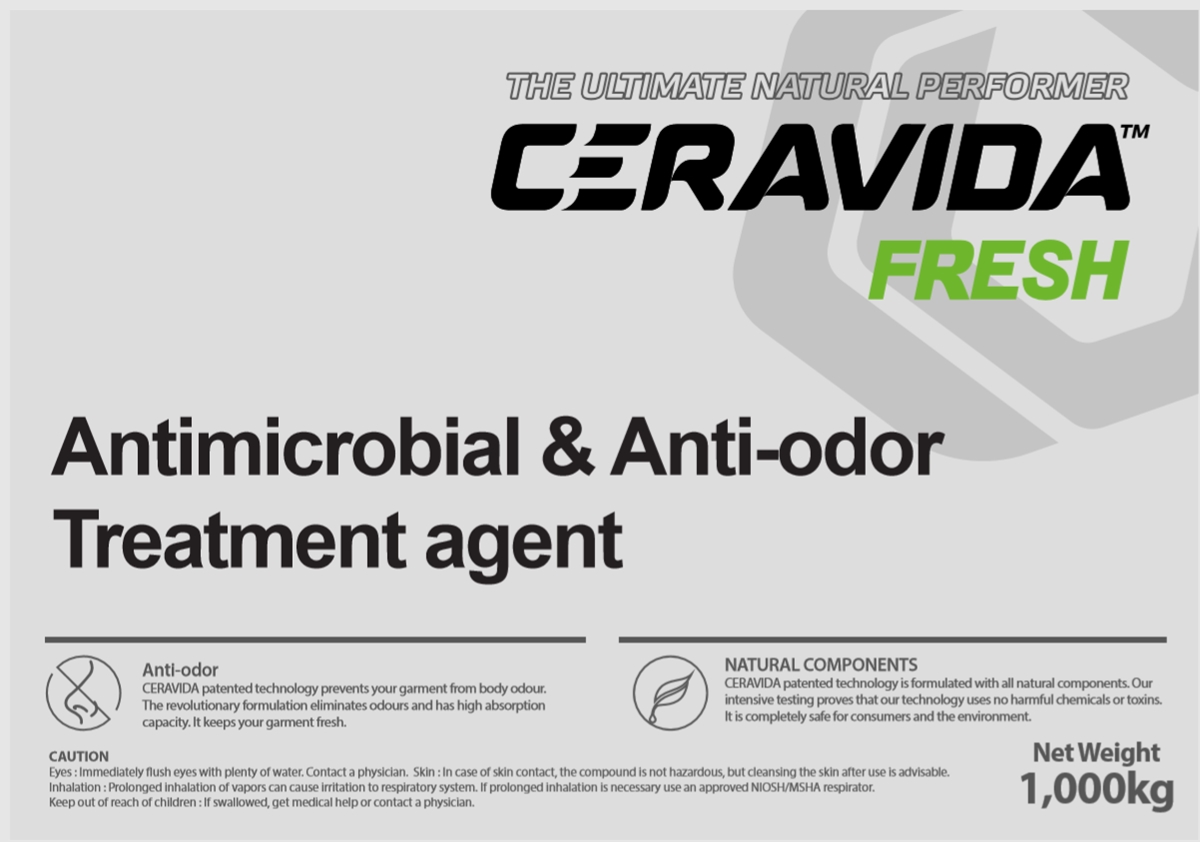 DRUG LABEL: CERAVIDA FRESH
NDC: 78543-100 | Form: LIQUID
Manufacturer: G.CLO CO., LTD
Category: otc | Type: HUMAN OTC DRUG LABEL
Date: 20201210

ACTIVE INGREDIENTS: POLIGLUSAM 5 kg/100 kg
INACTIVE INGREDIENTS: WATER; ACETIC ACID

Active Ingredient

Chitosan 5%

Purpose

Anti-Odor

Uses

Anti-odor treatment agents for all Textiles to prevents and removes odor molecules and microbes.

Inactive Ingredients

Acetic acid, Water

Eyes

Immediately flush eyes with plenty of water. Contact a physician.

Skin Inhalation

In case of skin contact, the compound is not Hazardous, but cleansing the skin after use is advisable.

Prolonged inhalation of vapors can cause irritation to respiratory system. If prolonged inhalation is necessary use an approved NIOSH/MSHA respirator.

Keep out of reach of children

If swallowed, get medical help or contact a physician.

Directions How to use

- Mix together in the proper proportion with the water in the tenter's water bath.

- Ceravida Fresh dosage is different depending on the tenter capacity.

- It must be sufficiently mixed with the water at a rate of about 5-10% dosage to process the fabric.

How to keep

It is recommended to store at room temperature where sunlight does not reach directly and in closed containers. The viscosity may increase during long-term storage, resulting in sediment. It is directly soluble in water.